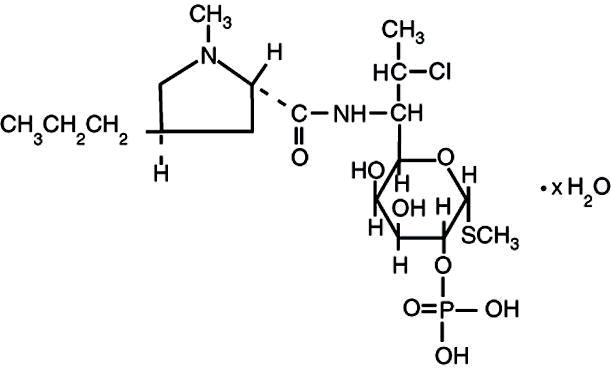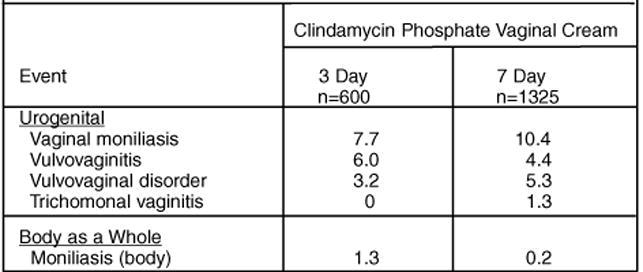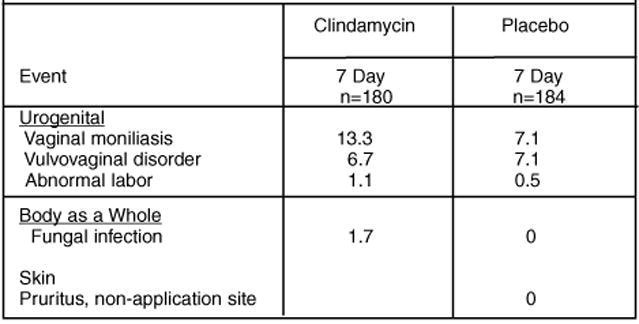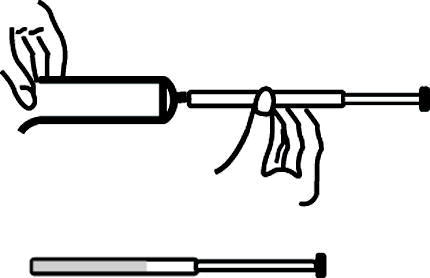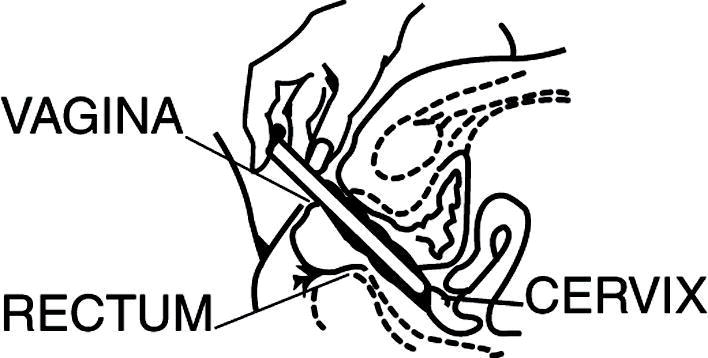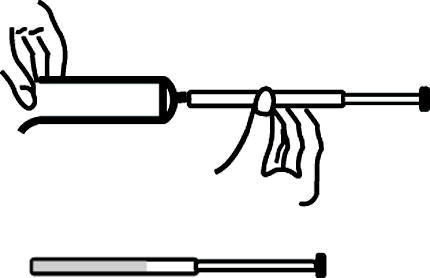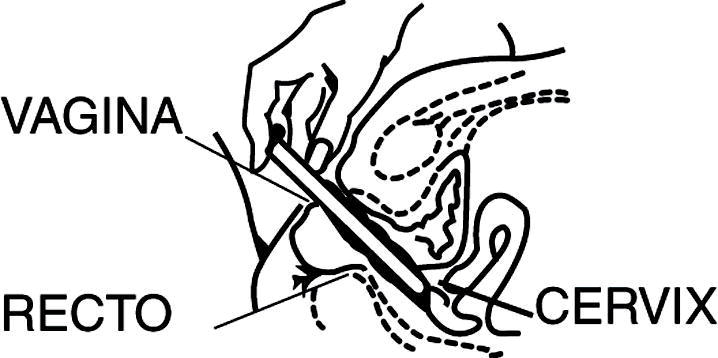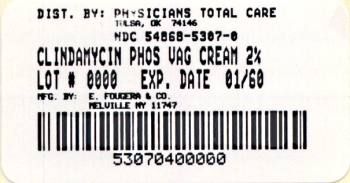 DRUG LABEL: Clindamycin Phosphate
NDC: 54868-5307 | Form: CREAM
Manufacturer: Physicians Total Care, Inc.
Category: prescription | Type: HUMAN PRESCRIPTION DRUG LABEL
Date: 20090831

ACTIVE INGREDIENTS: CLINDAMYCIN PHOSPHATE 20 mg/1 g
INACTIVE INGREDIENTS: BENZYL ALCOHOL; CETOSTEARYL ALCOHOL; CETYL PALMITATE; MINERAL OIL; POLYSORBATE 60; PROPYLENE GLYCOL; SORBITAN MONOSTEARATE; STEARIC ACID; WATER

CLINDAMYCIN PHOSPHATE VAGINAL CREAM USP, 2%

Rx only

FOR INTRAVAGINAL USE ONLY
NOT FOR OPHTHALMIC, DERMAL, OR ORAL USE

DESCRIPTION

Clindamycin phosphate is a water soluble ester of the semi-synthetic antibiotic produced by a 7(S)-chloro-substitution of the 7(R)-hydroxyl group of the parent antibiotic lincomycin. The chemical name for clindamycin phosphate is methyl 7-chloro-6,7,8-trideoxy-6-(1-methyl- trans-4-propyl-L-2-pyrrolidinecarboxamido)-1-thio-L-threo-α-D-galacto-octopyranoside 2-(dihydrogen phosphate). It has a molecular weight of 504.96, and the molecular formula is C18H34ClN2O8 PS. The structural formula is represented below:

Clindamycin phosphate vaginal cream 2%, is a semi-solid, white cream, which contains 2% clindamycin phosphate, USP, at a concentration equivalent to 20 mg clindamycin per gram. The pH of the cream is between 3.0 and 6.0. The cream also contains benzyl alcohol, cetostearyl alcohol, cetyl palmitate, mineral oil, polysorbate 60, propylene glycol, sorbitan monostearate, and stearic acid.

Each applicatorful of 5 grams of vaginal cream contains approximately 100 mg of clindamycin phosphate.

CLINICAL PHARMACOLOGY

Following a once a day intravaginal dose of 100 mg of clindamycin phosphate vaginal cream 2%, administered to 6 healthy female volunteers for 7 days, approximately 5% (range 0.6% to 11%) of the administered dose was absorbed systemically. The peak serum clindamycin concentration observed on the first day averaged 18 ng/mL (range 4 to 47 ng/mL) and on day 7 it averaged 25 ng/mL (range 6 to 61 ng/mL). These peak concentrations were attained approximately 10 hours post-dosing (range 4-24 hours).

Following a once a day intravaginal dose of 100 mg of clindamycin phosphate vaginal cream 2%, administered for 7 consecutive days to 5 women with bacterial vaginosis, absorption was slower and less variable than that observed in healthy females. Approximately 5% (range 2% to 8%) of the dose was absorbed systemically. The peak serum clindamycin concentration observed on the first day averaged 13 ng/mL (range 6 to 34 ng/mL) and on day 7 it averaged 16 ng/mL (range 7 to 26 ng/mL). These peak concentrations were attained approximately 14 hours post-dosing (range 4-24 hours).

There was little or no systemic accumulation of clindamycin after repeated vaginal dosing of clindamycin phosphate vaginal cream 2%. The systemic half-life was 1.5 to 2.6 hours.

MICROBIOLOGY

Clindamycin inhibits bacterial protein synthesis at the level of the bacterial ribosome. The antibiotic binds preferentially to the 50S ribosomal subunit and affects the process of peptide chain initiation. Although clindamycin phosphate is inactive in vitro, rapid in vivo hydrolysis converts this compound to the antibacterially active clindamycin.

Culture and sensitivity testing of bacteria are not routinely performed to establish the diagnosis of bacterial vaginosis. (See INDICATIONS AND USAGE.) Standard methodology for the susceptibility testing of the potential bacterial vaginosis pathogens, Gardnerella vaginalis, Mobiluncus spp., or Mycoplasma hominis, has not been defined. Nonetheless, clindamycin is an antimicrobial agent active in vitro against most strains of the following organisms that have been reported to be associated with bacterial vaginosis:

Bacteroides spp. | Mycoplasma hominis
Peptostreptococcus spp. | Gardnerella vaginalis
Mobiluncus spp.

INDICATIONS AND USAGE

Clindamycin phosphate vaginal cream 2%, is indicated in the treatment of bacterial vaginosis (formerly referred to as Haemophilus vaginitis, Gardnerella vaginitis, nonspecific vaginitis, Corynebacterium vaginitis, or anaerobic vaginosis). Clindamycin phosphate vaginal cream 2%, can be used to treat non-pregnant women and pregnant women during the second and third trimester. (See CLINICAL STUDIES.)

NOTE: For purposes of this indication, a clinical diagnosis of bacterial vaginosis is usually defined by the presence of a homogeneous vaginal discharge that (a) has a pH of greater than 4.5, (b) emits a "fishy" amine odor when mixed with a 10% KOH solution, and (c) contains clue cells on microscopic examination. Gram's stain results consistent with a diagnosis of bacterial vaginosis include (a) markedly reduced or absent Lactobacillus morphology, (b) predominance of Gardnerella morphotype, and (c) absent or few white blood cells.

Other pathogens commonly associated with vulvovaginitis, e.g., Trichomonas vaginalis, Chlamydia trachomatis, N. gonorrhoeae, Candida albicans, and Herpes simplex virus should be ruled out.

CONTRAINDICATIONS

Clindamycin phosphate vaginal cream 2%, is contraindicated in individuals with a history of hypersensitivity to clindamycin, lincomycin, or any of the components of this vaginal cream. Clindamycin phosphate vaginal cream 2%, is also contraindicated in individuals with a history of regional enteritis, ulcerative colitis, or a history of "antibiotic-associated" colitis.

WARNINGS

Pseudomembranous colitis has been reported with nearly all antibacterial agents, including clindamycin, and may range in severity from mild to life-threatening. Orally and parenterally administered clindamycin has been associated with severe colitis which may end fatally. Diarrhea, bloody diarrhea, and colitis (including pseudomembranous colitis) have been reported with the use of orally and parenterally administered clindamycin, as well as with topical (dermal) formulations of clindamycin. Therefore, it is important to consider this diagnosis in patients who present with diarrhea subsequent to the administration of clindamycin, even when administered by the vaginal route, because approximately 5% of the clindamycin dose is systemically absorbed from the vagina.

Treatment with antibacterial agents alters the normal flora of the colon and may permit overgrowth of clostridia. Studies indicate that a toxin produced by Clostridium difficile is a primary cause of "antibiotic-associated′′ colitis.

After the diagnosis of pseudomembranous colitis has been established, therapeutic measures should be initiated. Mild cases of pseudomembranous colitis usually respond to discontinuation of the drug alone. In moderate to severe cases, consideration should be given to management with fluids and electrolytes, protein supplementation, and treatment with an antibacterial drug clinically effective against Clostridium difficile colitis.

Onset of pseudomembranous colitis symptoms may occur during or after antimicrobial treatment.

PRECAUTIONS

General

Clindamycin phosphate vaginal cream 2%, contains ingredients that will cause burning and irritation of the eye. In the event of accidental contact with the eye, rinse the eye with copious amounts of cool tap water.

The use of clindamycin phosphate vaginal cream 2% may result in the overgrowth of nonsusceptible organisms in the vagina. In clinical studies involving 600 non-pregnant women who received treatment for 3 days, Candida albicans was detected, either symptomatically or by culture, in 8.8% of patients. In 9% of the patients, vaginitis was recorded. In clinical studies involving 1325 non-pregnant women who received treatment for 7 days, Candida albicans was detected, either symptomatically or by culture, in 10.5% of patients. Vaginitis was recorded in 10.7% of the patients. In 180 pregnant women who received treatment for 7 days, Candida albicans was detected, either symptomatically or by culture, in 13.3% of patients. In 7.2% of the patients, vaginitis was recorded. Candida albicans, as reported here, includes the terms: vaginal moniliasis and moniliasis (body as a whole). Vaginitis includes the terms: vulvo-vaginal disorder, vulvovaginitis, vaginal discharge, trichomonal vaginitis, and vaginitis.

Information for the Patient:

The patient should be instructed not to engage in vaginal intercourse, or use other vaginal products (such as tampons or douches) during treatment with this product.

The patient should also be advised that this cream contains mineral oil that may weaken latex or rubber products such as condoms or vaginal contraceptive diaphragms. Therefore, use of such products within 72 hours following treatment with clindamycin phosphate vaginal cream 2%, is not recommended.

Drug Interactions

Clindamycin has been shown to have neuromuscular blocking properties that may enhance the action of other neuromuscular blocking agents. Therefore, it should be used with caution in patients receiving such agents.

Carcinogenesis, Mutagenesis, Impairment of Fertility

Long term studies in animals have not been performed with clindamycin to evaluate carcinogenic potential. Genotoxicity tests performed included a rat micronucleus test and an Ames test. Both tests were negative. Fertility studies in rats treated orally with up to 300 mg/kg/day (31 times the human exposure based on mg/m^2) revealed no effects on fertility or mating ability.

Pregnancy: Teratogenic effects

Pregnancy Category B

There are no adequate and well-controlled studies in pregnant women during the first trimester of pregnancy. This drug should be used during the first trimester of pregnancy only if clearly needed.

Clindamycin phosphate vaginal cream 2% has been studied in pregnant women during the second trimester. In women treated for seven days, abnormal labor was reported in 1.1% of patients who received clindamycin vaginal cream 2% compared with 0.5% of patients who received placebo.

Reproduction studies have been performed in rats and mice using oral and parenteral doses of clindamycin up to 600 mg/kg/day (62 and 25 times, respectively, the maximum human exposure based on mg/m^2) and have revealed no evidence of harm to the fetus due to clindamycin. In one mouse strain, cleft palates were observed in treated fetuses; this outcome was not produced in other mouse strains or in other species and is, therefore, considered to be a strain specific effect.

See INDICATIONS AND USAGE; PRECAUTIONS, General; and ADVERSE REACTIONS.

Nursing Mothers

Clindamycin has been detected in human milk after oral or parenteral administration. It is not known if clindamycin is excreted in human milk following the use of vaginally administered clindamycin phosphate.

Because of the potential for serious adverse reactions in nursing infants from clindamycin phosphate, a decision should be made whether to discontinue nursing or to discontinue the drug, taking into account the importance of the drug to the mother.

Pediatric Use

Safety and effectiveness in pediatric patients have not been established.

Geriatric Use:

Clinical studies for clindamycin phosphate vaginal cream 2% did not include sufficient numbers of subjects aged 65 and over to determine whether they respond differently from younger subjects. Other reported clinical experience has not identified differences in responses between the elderly and younger patients.

ADVERSE REACTIONS

Clinical trials

Non-pregnant Women: In clinical trials involving non-pregnant women, 1.8% of 600 patients who received treatment with clindamycin phosphate vaginal cream 2% for 3 days and 2.7% of 1325 patients who received treatment for 7 days discontinued therapy due to drug-related adverse events. Medical events judged to be related, probably related, possibly related, or of unknown relationship to vaginally administered clindamycin phosphate vaginal cream 2%, were reported for 20.7% of the patients receiving treatment for 3 days and 21.3% of the patients receiving treatment for 7 days. Events occurring in ≥1% of patients receiving clindamycin phosphate vaginal cream 2% are shown in Table 1.

Events Occuring in ≥ 1% of Non-pregnant Patients Receiving Clindamycin Phosphate Vaginal Cream 2%

Other events occurring in <1% of the clindamycin vaginal cream 2% groups include:

Urogenital system: vaginal discharge, metrorrhagia, urinary tract infection, endometriosis, menstrual disorder, vaginitis/vaginal infection, and vaginal pain.

Body as a whole: localized abdominal pain, generalized abdominal pain, abdominal cramps, halitosis, headache, bacterial infection, inflammatory swelling, allergic reaction, and fungal infection.

Digestive system: nausea, vomiting, constipation, dyspepsia, flatulence, diarrhea, and gastrointestinal disorder.

Endocrine system: hyperthyroidism.

Central nervous system: dizziness and vertigo.

Respiratory system: epistaxis.

Skin: pruritus (non-application site), moniliasis, rash, maculopapular rash, erythema, and urticaria.

Special senses: taste perversion.

Pregnant Women: In a clinical trial involving pregnant women during the second trimester, 1.7% of 180 patients who received treatment for 7 days discontinued therapy due to drug-related adverse events. Medical events judged to be related, probably related, possibly related, or of unknown relationship to vaginally administered clindamycin phosphate vaginal cream 2%, were reported for 22.8% of pregnant patients. Events occurring in ≥1% of patients receiving either clindamycin phosphate vaginal cream 2% or placebo are shown in Table 2.

Events Occuring in ≥ 1% of Pregnant Patients Receiving Clindamycin Phosphate Vaginal Cream 2% or Placebo

Other events occurring in <1% of the clindamycin vaginal cream 2% group include:

Urogenital system: dysuria, metrorrhagia, vaginal pain, and trichomonal vaginitis.

Body as a whole: upper respiratory infection.

Skin: pruritus (topical application site) and erythema.

Other clindamycin formulations:

Clindamycin vaginal cream affords minimal peak serum levels and systemic exposure (AUCs) of clindamycin compared to 100 mg oral clindamycin dosing. Although these lower levels of exposure are less likely to produce the common reactions seen with oral clindamycin, the possibility of these and other reactions cannot be excluded presently. Data from well-controlled trials directly comparing clindamycin administered orally to clindamycin administered vaginally are not available.

The following adverse reactions and altered laboratory tests have been reported with the oral or parenteral use of clindamycin:

Gastrointestinal: Abdominal pain, esophagitis, nausea, vomiting, and diarrhea. (See WARNINGS.)

Hematopoietic: Transient neutropenia (leukopenia), eosinophilia, agranulocytosis, and thrombocytopenia have been reported. No direct etiologic relationship to concurrent clindamycin therapy could be made in any of these reports.

Hypersensitivity Reactions: Maculopapular rash and urticaria have been observed during drug therapy. Generalized mild to moderate morbilliform-like skin rashes are the most frequently reported of all adverse reactions. Rare instances of erythema multiforme, some resembling Stevens-Johnson syndrome, have been associated with clindamycin. A few cases of anaphylactoid reactions have been reported. If a hypersensitivity reaction occurs, the drug should be discontinued.

Liver: Jaundice and abnormalities in liver function tests have been observed during clindamycin therapy.

Musculoskeletal: Rare instances of polyarthritis have been reported.

Renal: Although no direct relationship of clindamycin to renal damage has been established, renal dysfunction as evidenced by azotemia, oliguria, and/or proteinuria has been observed in rare instances.

OVERDOSAGE

Vaginally applied clindamycin phosphate vaginal cream 2% could be absorbed in sufficient amounts to produce systemic effects. (See WARNINGS.)

DOSAGE AND ADMINISTRATION

The recommended dose is one applicatorful of clindamycin phosphate vaginal cream 2%, (5 grams containing approximately 100 mg of clindamycin phosphate) intravaginally, preferably at bedtime, for 3 or 7 consecutive days in non-pregnant patients and for 7 consecutive days in pregnant patients. (See CLINICAL STUDIES.)

HOW SUPPLIED

Clindamycin Phosphate Vaginal Cream 2% (clindamycin phosphate vaginal cream) is a white to off-white cream having a slight odor and is supplied as follows:

40 g tube (with 7 disposable applicators) NDC 54868-5307-0

Store at 20° to 25°C (68° to 77° F)[see USP Controlled Room Temperature].

CLINICAL STUDIES

In two clinical studies involving 674 evaluable non-pregnant women with bacterial vaginosis comparing clindamycin phosphate vaginal cream 2% for 3 or 7 days, the clinical cure rates, determined at 1 month posttherapy, ranged from 72% to 81% for the 3-day treatment and 84% to 86% for the 7-day treatment.

 | Clindamycin Phosphate 3 Day | Clindamycin Phosphate 7 Day
U.S. Study | 94/131 | 72% | 110/128 | 86%
European Study | 161/199 | 81% | 181/216 | 84%

In a clinical study involving 249 evaluable pregnant patients in the second and third trimester treated for 7 days, the clinical cure rate, determined at 1 month posttherapy, was 60% (77/129) in the clindamycin arm and 9% (11/120) for the vehicle arm. The determination of clinical cure was based on the absence of a "fishy" amine odor when the vaginal discharge was mixed with a 10% KOH solution and the absence of clue cells on microscopic examination.

E. FOUGERA & CO.
A division of Nycomed US Inc.
Melville, New York 11747

I2277
R4/08
#116

Relabeling of "Additional Barcode Label" by:
Physicians Total Care, Inc.
Tulsa, OK 74146

DIRECTIONS FOR USE

7 Disposable plastic applicators are provided with this package. They are designed to allow proper vaginal administration of the cream.

Remove cap from cream tube. Screw a plastic applicator on the threaded end of the tube.

Rolling tube from the bottom, squeeze gently and force the medication into the applicator.

The applicator is filled when the plunger reaches its predetermined stopping point.

Unscrew the applicator from the tube and replace the cap.

While lying on your back, firmly grasp the applicator barrel and insert into vagina as far as possible without causing discomfort.

Slowly push the plunger until it stops. Carefully withdraw applicator from vagina, and discard applicator.

REMEMBER TO APPLY ONE APPLICATORFUL EACH NIGHT BEFORE BEDTIME, OR AS PRESCRIBED BY YOUR DOCTOR.

INSTRUCCIONES PARA LA PACIENTE

Este envase contiene 7 aplicadores de plástico desechables. Los aplicadores están diseñados para la adminstración apropiada de la crema en la vagina.

Remueva la tapa del tubo de crema y enrosque el aplicador de plástico al tubo.

Exprima el tubo suavemente desde el extremo inferior y fuerce el medicamento al aplicador.

El aplicador estará lleno cuando el émbolo llega a su máxima longitud. Desenrosque el aplicador del tubo y vuelva a poner la tapa.

Acuéstese de espada y agarrando firemente el aplicador, introdúzcalo en la vagina tanto como sea posible sin causar molestias.

Empuje lentamente el émbolo hasta que se detenga.

Saque el aplicador cuidadosamente de la vagina y descártelo.

RECUERDE APLICARSE UN APLICADOR LLENO TODAS LAS NOCHES AL ACOSTARSE, O DE ACUDERDO CON LAS INDICACIONES DE SU MEDICO.

PACKAGE LABEL – PRINCIPAL DISPLAY PANEL – 40 GRAM CARTON

CLINDAMYCIN
PHOSPHATE
VAGINAL CREAM
USP, 2%
equivalent to 2% clindamycin

For Intravaginal Use Only.
Not for Ophthalmic,
Dermal, or Oral Use.

Rx only

NET WT 40 grams
with
7 applicators